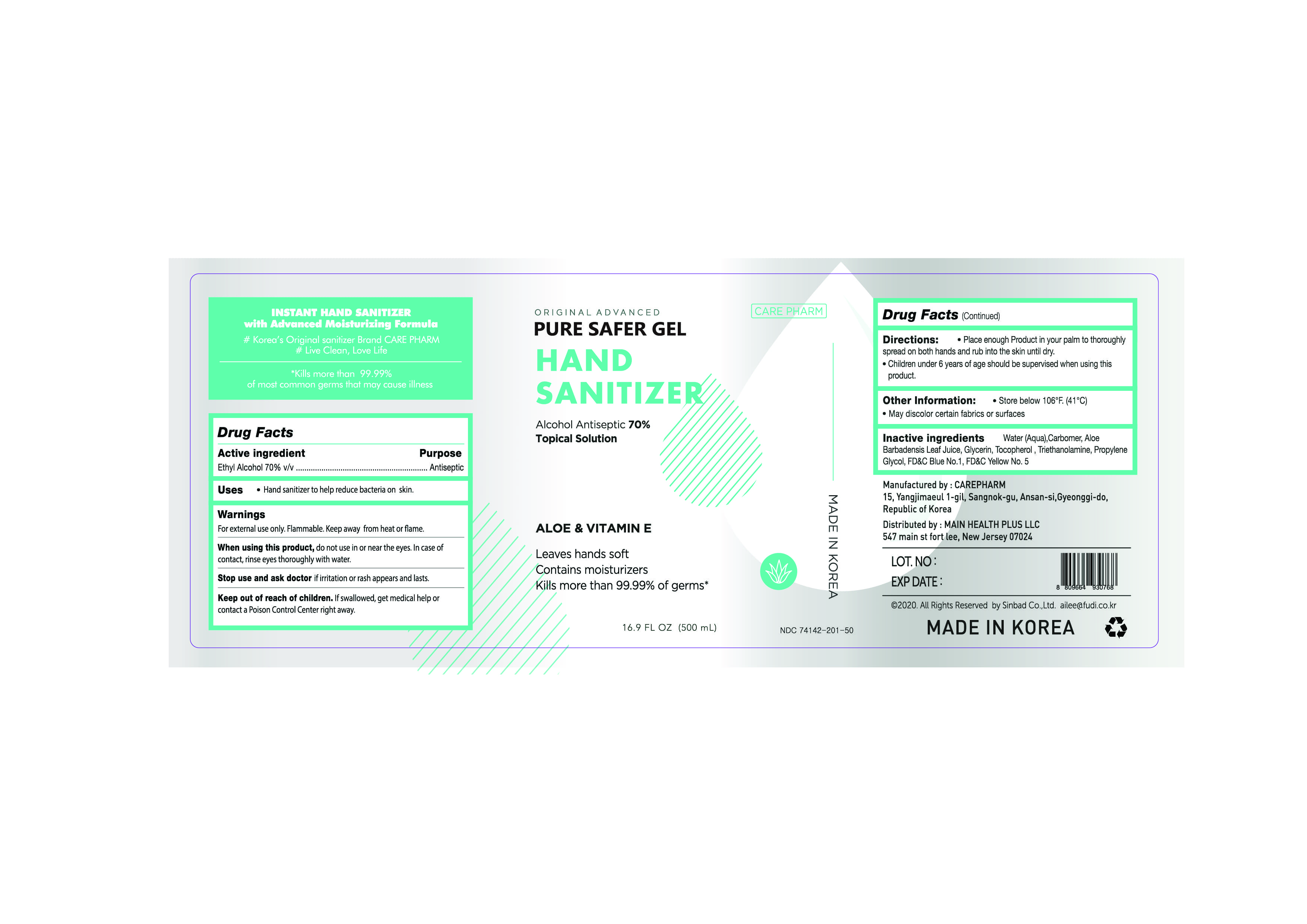 DRUG LABEL: Pure Safer Gel(Ethanol)
NDC: 74142-201 | Form: GEL
Manufacturer: Sinbad Co.,Ltd
Category: otc | Type: HUMAN OTC DRUG LABEL
Date: 20200525

ACTIVE INGREDIENTS: ALCOHOL 65.6 mL/100 mL
INACTIVE INGREDIENTS: PROPYLENE GLYCOL; ALOE; TOCOPHEROL; CARBOMER HOMOPOLYMER TYPE B (ALLYL PENTAERYTHRITOL CROSSLINKED); FD&C BLUE NO. 1; FD&C YELLOW NO. 5; TROLAMINE; GLYCERIN; WATER

Active ingredient

Ethyl Alcohol 70.0% v/v

Purpose

Antiseptic

Uses

Hand sanitizer to help reduce bacteria on skin.

Warnings

For extrnal use only. Flammable. Keep away from heat or flame.

When using this product, do not use in or near the eyes. In case of contact, rinse eyes thoroughly with water.

Stop use and ask doctor if iffitation or rash appears and lasts.

Keep out of reach of children. If swallowed, get medical help or contact a Poison Control Center right away.

Inactive ingredients

Water(Aqua), Carbomer, Aloe Barbadensis Leaf Juice, Glycerin, Tocopherol, Triethanolamine, Propylene Glycol, FD&C Blue No.1, FD&C Yellow No.5

Directions:

- Place enough Product in your palm to thoroughly spread on both hands and rub into the skin until dry.
- Children under 6 years of age should be supervised when using this product.

Other Information:

- Store below 106°F. (41°C)
- May discolor certain fabrics or surfaces.